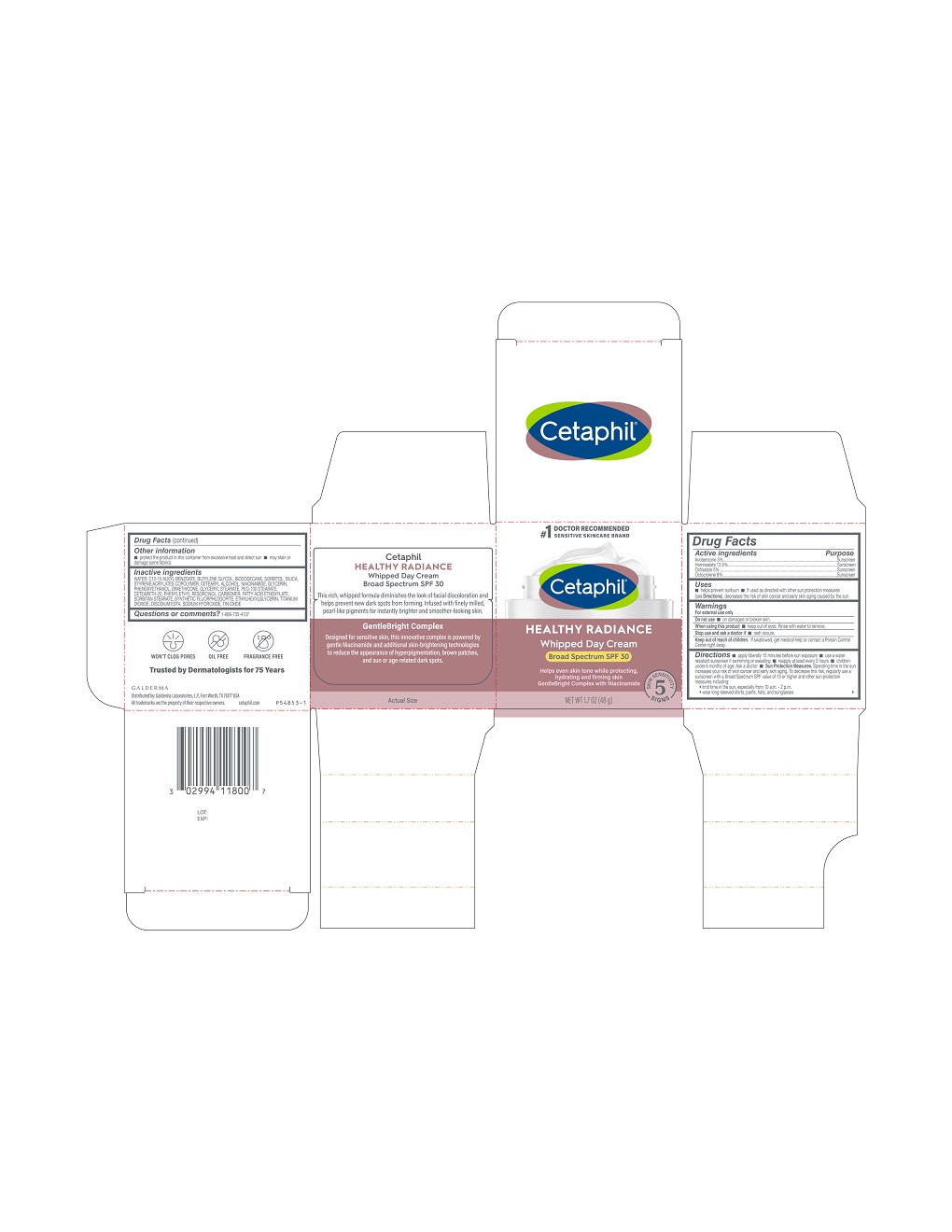 DRUG LABEL: Cetaphil Healthy Radiance Whipped Day Cream Broad Spectrum SPF 30
NDC: 0299-4118 | Form: LOTION
Manufacturer: Galderma Laboratories, L.P.
Category: otc | Type: HUMAN OTC DRUG LABEL
Date: 20231128

ACTIVE INGREDIENTS: Avobenzone 30 mg/1 g; Homosalate 125 mg/1 g; Octisalate 50 mg/1 g; Octocrylene 80 mg/1 g
INACTIVE INGREDIENTS: Water; Alkyl (C12-15) Benzoate; Butylene Glycol; Isododecane; Sorbitol; Silicon Dioxide; Styrene/Acrylamide Copolymer (500000 Mw); Cetostearyl Alcohol; Niacinamide; Glycerin; Phenoxyethanol; Dimethicone; Glyceryl Monostearate; Peg-100 Stearate; Polyoxyl 20 Cetostearyl Ether; Phenylethyl Resorcinol; Carbomer Homopolymer, Unspecified Type; Sorbitan Monostearate; Magnesium Potassium Aluminosilicate Fluoride; Ethylhexylglycerin; Titanium Dioxide; Edetate Disodium Anhydrous; Sodium Hydroxide; Stannic Oxide

Drug Facts

Active Ingredients.....Purpose

Avobenzone 3% .................Sunscreen
Homosalate 12.5% .........… Sunscreen
Octisalate 5% ...............… Sunscreen
Octocrylene 8% ................. Sunscreen

Purpose

Sunscreen

Uses

- helps prevent sunburn
- if used as directed with other sun protection measures (see Directions), decreases the risk of skin cancer and early skin aging caused by the sun

Warnings

For external use only

Do not use

▪ on damaged or broken skin

When using this product

• keep out of eyes. Rinse with water to remove.

Stop use and ask a doctor if

• rash occurs.

Keep out of reach of children.

If swallowed, get medical help or contact a Poison Control Center right away.

Directions

- apply liberally 15 minutes before sun exposure
- use a water resistant sunscreen if swimming or sweating
- reapply at least every 2 hours
- children under 6 months of age: Ask a doctor
- Sun Protection Measures. Spending time in the sun increases your risk of skin cancer and early skin aging. To decrease this risk, regularly use a sunscreen with a Broad Spectrum SPF value of 15 or higher and other sun protection measures including:
- limit time in the sun, especially from 10 a.m. - 2 p.m.
- wear long-sleeved shirts, pants, hats, and sunglasses

Other information

- protect the product in this container from excessive heat and direct sun
- may stain or damage some fabrics

Inactive Ingredients

Water, C12-15 Alkyl Benzoate, Butylene Glycol, Isododecane, Sorbitol, Silica, Styrene/Acrylates Copolymer, Cetearyl Alcohol, Niacinamide, Glycerin, Phenoxyethanol, Dimethicone, Glyceryl Stearate, PEG-100 Stearate, Ceteareth-20, Phenylethyl Resorcinol, Carbomer, Fatty Acid Ethoxylate, Sorbitan Stearate, Synthetic Fluorphlogopite, Ethylhexylglycerin, Titanium Dioxide, Disodium EDTA, Sodium Hydroxide, Tin Oxide

Questions or comments?

1-866-735-4137

Principal Display Panel - 3 FL OZ Carton

#1 Doctor Recommended
Sensitive Skincare Brand
Cetaphil®
HEALTHY RADIANCE

Whipped Day Cream
Broad Spectrum SPF 30
Helps even skin tone while protecting,
hydrating and firming skin
GentleBright Complex with Niacinamide
Five Skin Sensitivity Signs
NET WT 1.7 OZ (48 g)

Distributed by:
Galderma Laboratories, L.P., Fort Worth, TX 76177 USA
All trademarks are the property of their respective owners.
Cetaphil.com
P54853-1